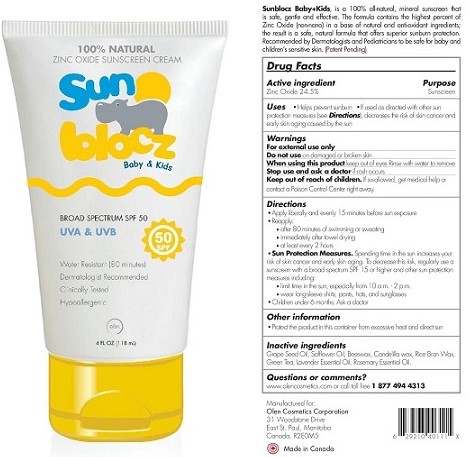 DRUG LABEL: Sunblocz Baby and Kids
NDC: 52358-0003 | Form: CREAM
Manufacturer: Olen Skin Care Corporation
Category: otc | Type: HUMAN OTC DRUG LABEL
Date: 20241029

ACTIVE INGREDIENTS: ZINC OXIDE 28.9 g/118 mL
INACTIVE INGREDIENTS: CANDELILLA WAX; SAFFLOWER OIL; YELLOW WAX; RICE BRAN; LAVENDER OIL; GRAPE SEED OIL; GREEN TEA LEAF; ROSEMARY OIL

Sunblocz Baby & Kids

Drug Facts

Active ingredient

Zinc Oxide 24.5%

Purpose

Sunscreen

Uses

- Helps prevent sunburn
- If used as directed with other sun protection measures (see Directions), decreases the risk of skin cancer and early skin aging caused by the sun

Warnings

For external use only

Do not use on damaged or broken skin

When using this product keep out of eyes. Rinse with water to remove.

Stop use and ask a doctor if rash occurs.

Keep out of reach of children. If swallowed, get medical help or contact a Poison Control Center right away.

Directions

- Apply liberally and evenly 15 minutes before sun exposure
- Reapply:
- after 80 minutes of swimming or sweating
- immediately after towel drying
- at least every 2 hours
- Sun Protection Measures. Spending time in the sun increases your risk of skin cancer and early skin aging. To decrease this risk, regularly use a sunscreen with a broad spectrum SPF 15 or higher and other sun protection measures including:
- limit time in the sun, especially from 10 a.m. -2 p.m.
- wear long-sleeve shirts, pants, hats and sunglasses
- Children under 6 months: Ask a doctor

Other information

- Protect the product in this container from excessive heat and direct sun

Inactive ingredients

Grape Seed Oil, Safflower Oil, Beeswax, Candelilla wax, Rice Bran Wax, Green Tea, Lavender Essential Oil, Rosemary Essential Oil.

Questions or comments?

www.olencosmetics.com or call toll free 1-877-494-4313

Manufactured for:

Olen Cosmetics Corporation

31 Woodstone Drive

East St. Paul, Manitoba

Canada, R2EOM5

Made in Canada

PACKAGE LABEL

100% NATURAL

ZINC OXIDE SUNSCREEN CREAM

Sunblocz Baby & Kids

BROAD SPECTRUM SPF 50

UVA & UVB

Water Resistant (80 minutes)

Dermatologist Recommended

Clinically Tested

Hypoallergenic

4 FL OZ (118 mL)